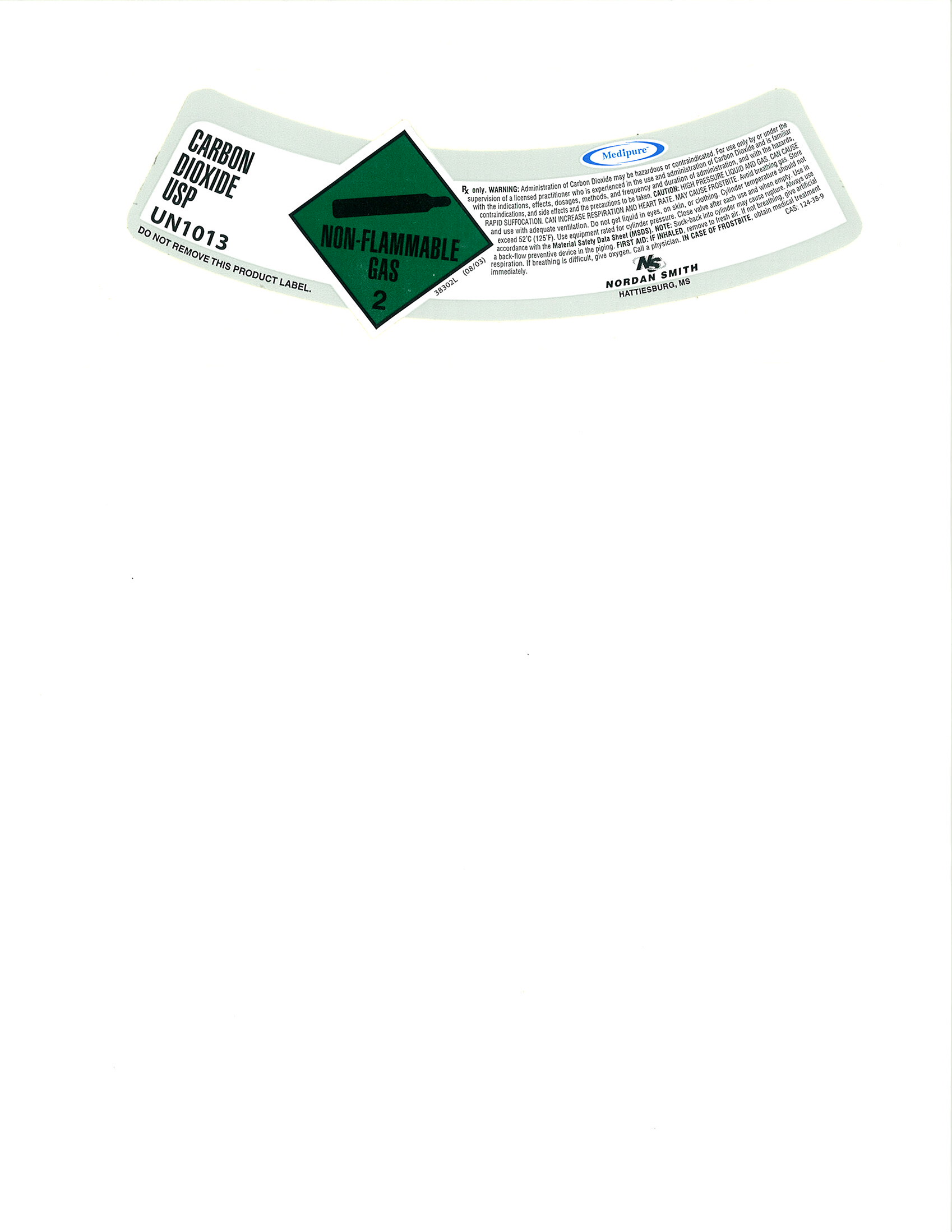 DRUG LABEL: Carbon Dioxide
NDC: 54416-003 | Form: GAS
Manufacturer: Nordan Smith Welding Supply
Category: prescription | Type: HUMAN PRESCRIPTION DRUG LABEL
Date: 20100813

ACTIVE INGREDIENTS: Carbon Dioxide 990 mL/1 L

Carbon Dioxide

PACKAGE LABEL

CARBON DIOXIDE USP
UN1013
DO NOT REMOVE THIS PRODUCT LABEL.
NON-FLAMMABLE GAS 2
Medipure
RX only. WARNING: administration of Carbon Dioxide may be hazardous or contraindicated. For use only by or under the supervision of a licensed practitioner who is experienced in the use and administration of Carbon Dioxide and is familiar with the indications, effects, dosages, methods, and frequency and duration of administration, and with the hazards, contraindications, and side effects and the precautions to be taken. CAUTION: HIGH PRESSURE LIQUID AND GAS. CAN CAUSE RAPID SUFFOCATION. CAN INCREASE RESPIRATION AND HEART RATE. MAY CAUSE FROSTBITE. Avoid breathing gas. Store and use with adequate ventilation. Do not get liquid in eyes, on skin, or clothing. Cylinder temperature should not exceed 52°C (125°F). Use equipment rated for cylinder pressure. Close valve after each use and when empty. Use in accordance with the Material Safety Data Sheet (MSDS). NOTE: Suck-back into cylinder may cause rupture. Always use a back-flow preventive device in the piping. FIRST AID: IF INHALED, remove to fresh air. If not breathing, give artificial respiration. If breathing is difficult, give oxygen. Call a physician. IN CASE OF FROSTBITE, obtain medical treatment immediately.
N/S NORDAN SMITH HATTIESBURG, MS. CAS:124-38-9
38302L (08/03)